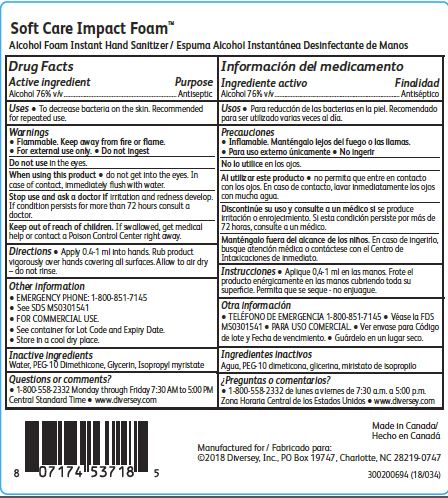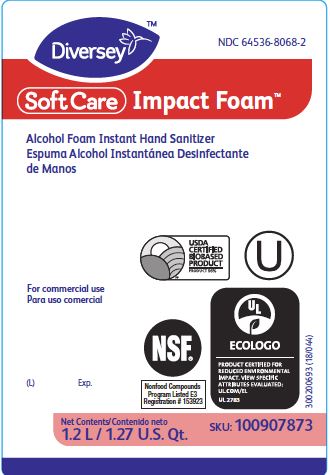 DRUG LABEL: Soft Care Impact Foam Alcohol Foam Instant Hand Sanitizer
NDC: 64536-8068 | Form: LIQUID
Manufacturer: Diversey, Inc.
Category: otc | Type: HUMAN OTC DRUG LABEL
Date: 20241216

ACTIVE INGREDIENTS: ALCOHOL 76 L/100 L
INACTIVE INGREDIENTS: WATER; PEG-10 DIMETHICONE (600 CST); GLYCERIN; ISOPROPYL MYRISTATE

Drug Facts

Active ingredient

Alcohol 76% v/v

Purpose

Antiseptic

Uses

To decrease bacteria on the skin.

Recommended for repeated use.

Warnings

Flammable. Keep away from fire or flame.

For external use only.

Do not ingest.

Do not use in the eye.

When using this product do not get into the eyes.

In case of contact, immediately flush with water.

Stop use and ask a doctor if irritation and redness develop.

If condition persists for more than 72 hours consult a doctor.

Keep out of reach of children.

If swallowed, get medical help or contact a Poison control Center right away.

Directions

Apply 0.4-1 ml into hands.

Rub product vigorously over hands covering all surfaces.

Allow to air dry - do not rinse.

Other information

EMERGENCY PHONE: 1-800-851-7145

See SDS MS0301541

FOR COMMERCIAL USE.

See container for Lot Code and Expiry Date.

Store in a cool dry place.

Inactive ingredients

Water, PEG-10 Dimethicone, Glycerin, Isopropyl myristate

Questions or comments?

1-800-558-2332 Monday through Friday 7:30 to 5:00 PM Central Standard Time

www.diversey.com

PACKAGE LABEL

NDC 64536-8068-2

Diversey

SoftCare Impact Foam

Alcohol Foam Instant Hand Sanitizer

For commercial use

USDA CERTIFIED BIOBASED PRODUCT Product 96%

U

(L) Exp.

NSF

Nonfood Compounds

Program Listed E3

Registration # 153923

UL ECOLOGO

Net Contents

1.2 L/1.27 U.S. Qt.

SKU: 100907873